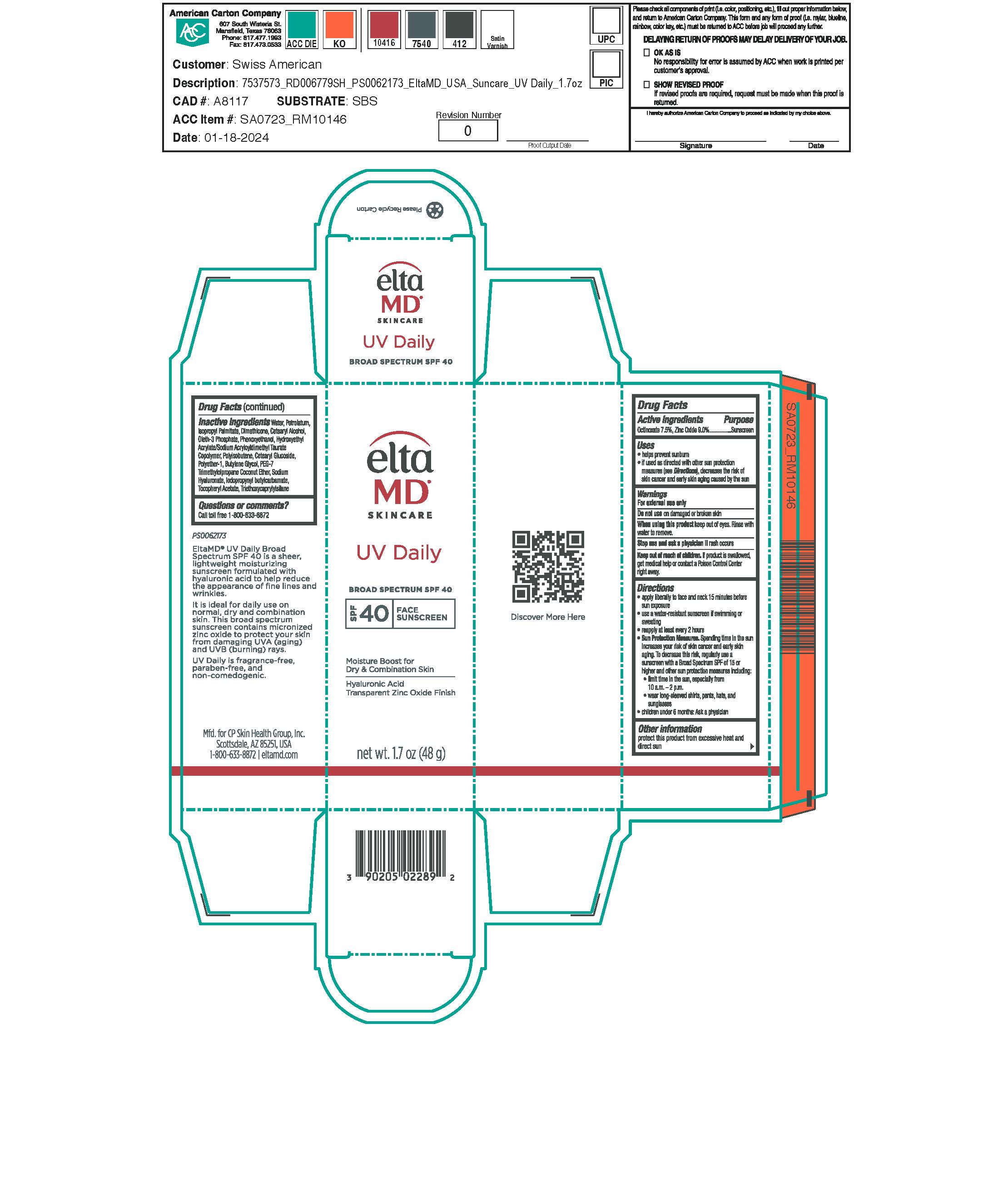 DRUG LABEL: EltaMD UV Daily
NDC: 72043-6804 | Form: LOTION
Manufacturer: CP Skin Health Group, Inc
Category: otc | Type: HUMAN OTC DRUG LABEL
Date: 20250331

ACTIVE INGREDIENTS: ZINC OXIDE 90 g/1000 g; OCTINOXATE 75 g/1000 g
INACTIVE INGREDIENTS: WATER; .ALPHA.-TOCOPHEROL ACETATE; CETOSTEARYL ALCOHOL; PHENOXYETHANOL; PETROLATUM; DIMETHICONE; ISOPROPYL PALMITATE; OLETH-3 PHOSPHATE; TRIETHOXYCAPRYLYLSILANE; CETEARYL GLUCOSIDE; CITRIC ACID MONOHYDRATE; HYALURONIC ACID; HYDROXYETHYL ACRYLATE/SODIUM ACRYLOYLDIMETHYL TAURATE COPOLYMER (100000 MPA.S AT 1.5%); POLYISOBUTYLENE (1000 MW); PEG-7 TRIMETHYLOLPROPANE COCONUT ETHER; BUTYLENE GLYCOL; IODOPROPYNYL BUTYLCARBAMATE

EltaMD UV Daily

Warnings

For external use only. Do not use on damaged or broken skin. When using this product keep out of eyes. Rinse with water to remove. Stop use and ask a physician if rash occurs. If product is swallowed get medical help or contact a Poison Control Center right away.

Active ingredients

Octinoxate 7.5% Sunscreen
Zinc Oxide 9.0% Sunscreen

Indications & Uses:

Helps prevent sunburn. If used as directed with other sun protection measure (See Directions), decreases the risk of skin cancer and early skin aging caused by the sun.

Purpose

Helps prevent sunburn. If used as directed with other sun protection measure (See Directions), decreases the risk of skin cancer and early skin aging caused by the sun.

Keep out of reach of children

Directions:

Apply liberally 15 minutes before sun exposure. Use a water-resistant sunscreen if swimming or sweating. Reapply at least every 2 hours. Sun Protection Measures: Spending time in the sun increases your risk of skin cancer and early skin aging. To decrease this risk, regularly use a sunscreen with a broad-spectrum SPF of 15 or higher and other sun protection measures including: limit time in the sun, especially from 10 am to 2 pm. Wear long-sleeve shirts, pants, hats, and sunglasses. Children under 6 months: ask a physician.

Other information:

Protect this product from excessive heat and direct sun.

Inactive ingredients

water, petrolatum, isopropyl palmitate, dimethicone, cetearyl alcohol, oleth-3 phosphate, phenoxyethanol, hydroxyethyl acrylate/sodium acryloyldimethyl taurate copolymer, polyisobutene, cetearyl glucoside, polyether-1, butylene glycol, PEG-7 trimethylolpropane coconut ether, sodium hyaluronate, iodopropynyl butylcarbamate, tocopheryl acetate, triethoxycaprylylsilane

Questions?

Call toll free 1-800-633-8872